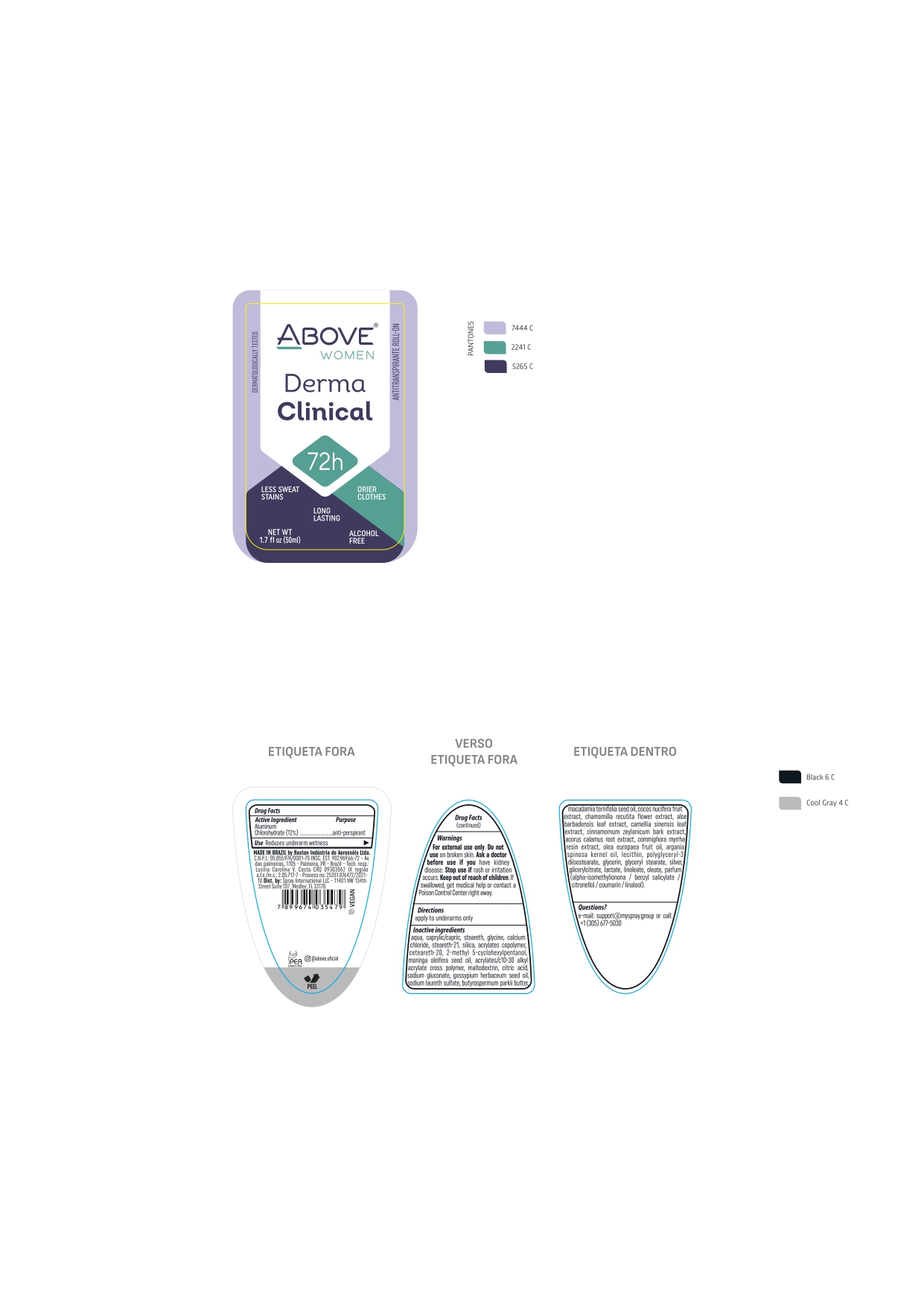 DRUG LABEL: ABOVE WOMEN DERMA CLINICAL 72 H
NDC: 73306-1138 | Form: CREAM
Manufacturer: BASTON INDUSTRIA DE AEROSSOIS LTDA
Category: otc | Type: HUMAN OTC DRUG LABEL
Date: 20241226

ACTIVE INGREDIENTS: ALUMINUM CHLOROHYDRATE 12 mg/100 g
INACTIVE INGREDIENTS: MEDIUM-CHAIN TRIGLYCERIDES

ABOVE WOMEN DERMA CLINICAL 72 H